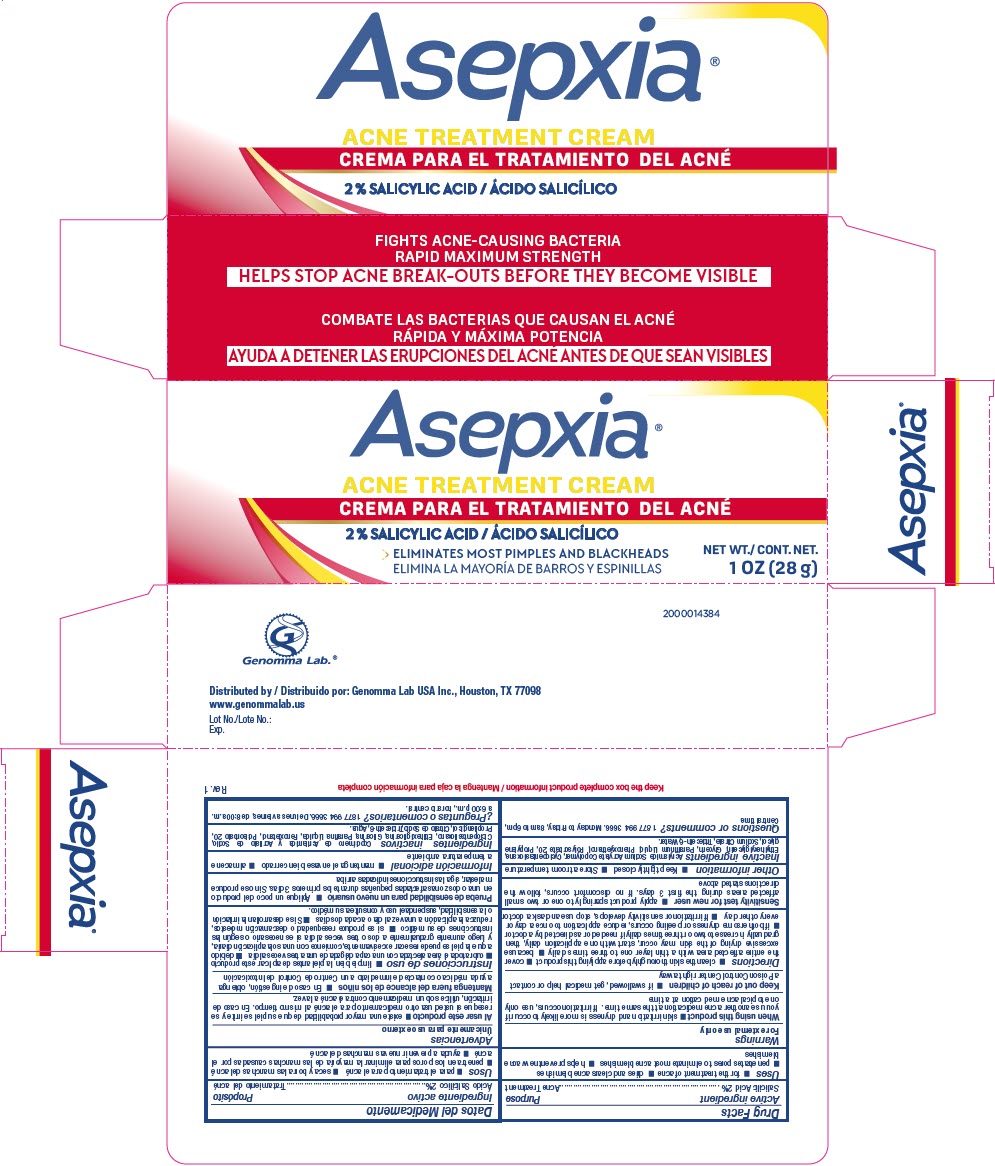 DRUG LABEL: Asepxia Acne Treatment
NDC: 50066-064 | Form: CREAM
Manufacturer: Genomma Lab USA
Category: otc | Type: HUMAN OTC DRUG LABEL
Date: 20241008

ACTIVE INGREDIENTS: SALICYLIC ACID 20 mg/1 g
INACTIVE INGREDIENTS: CYCLOMETHICONE 5; WATER; PROPYLENE GLYCOL; GLYCERIN; POLYSORBATE 20; PHENOXYETHANOL

Asepxia® Acne Treatment Cream

Drug Facts

Active ingredient

Salicilic Acid 2%

Purpose

Acne Treatment

Uses

- for the treatment of acne
- dries and clears acne blemishes
- penetrates pores to eliminate most acne blemishes
- helps prevent new acne blemishes

Warnings

For external use only

When using this product

- skin irritation and dryness is more likely to occur if you use another acne medication at the same time. If irritation occurs, use only one topical acne med cation at a time

Keep out of reach of children

- if swallowed, get medical help or contact a Poison Control Center right away

Directions

- clean the skin thoroughly before applying this product
- cover the entire affected area with a thin layer one to three times daily
- because excessive drying of the skin may occur, start with one application daily, then gradually increase to two or three times daily if needed or as directed by a doctor
- if bothersome dryness or peeling occurs, reduce application to once a day or every other day
- If irritation or sensitivity develops, stop use and ask a doctor

Sensitivity test for new user

- apply product sparingly to one or two small affected areas during the first 3 days. If no discomfort occurs, follow the directions stated above

Other information

- Keep tightly closed
- Store at room temperature

Inactive ingredients

Acrylamide Sodium Acrylate Copolymer, Cyclopentasiloxane, Ethylhexylglycerin, Glycerin, Paraffinum Liquid, Phenoxyethanol, Polysorbate 20, Propylene glycol, Sodium Citrate, Trideceth-6, Water.

Questions or comments?

1 877 994 3666. Monday to Friday, 8am to 6pm, Central time.

Distributed by: Genomma Lab USA Inc., Houston, TX 77098

PRINCIPAL DISPLAY PANEL - 28 g Tube Carton

Asepxia®

ACNE TREATMENT CREAM

2 % SALICYLIC ACID

ELIMINATES MOST PIMPLES AND BLACKHEADS

NET WT.
1 OZ (28 g)